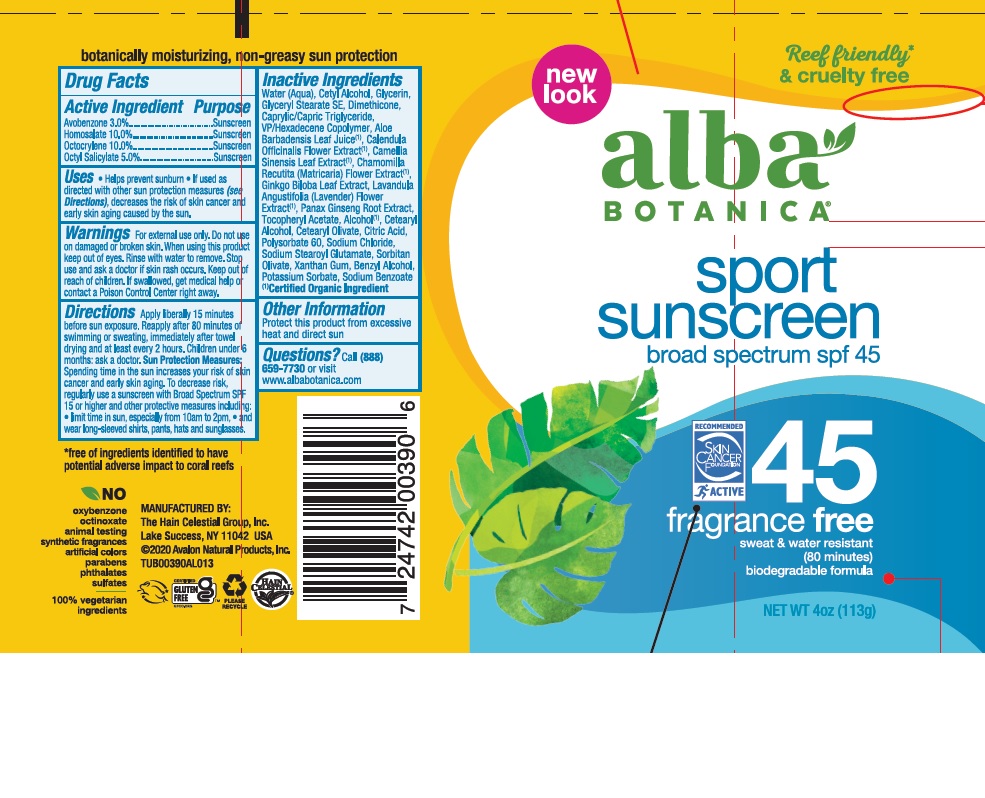 DRUG LABEL: AL0039006 Alba Sport Sunscreen Fragrance Free SPF45
NDC: 61995-2090 | Form: LOTION
Manufacturer: The Hain Celestial Group, Inc.
Category: otc | Type: HUMAN OTC DRUG LABEL
Date: 20210412

ACTIVE INGREDIENTS: HOMOSALATE 10 g/100 g; OCTISALATE 5 g/100 g; OCTOCRYLENE 10 g/100 g; AVOBENZONE 3 g/100 g
INACTIVE INGREDIENTS: CETYL ALCOHOL; ALCOHOL; BENZYL ALCOHOL; ALOE VERA LEAF; GLYCERIN; CITRIC ACID MONOHYDRATE; WATER; VINYLPYRROLIDONE/HEXADECENE COPOLYMER; SODIUM STEAROYL GLUTAMATE; .ALPHA.-TOCOPHEROL ACETATE; GLYCERYL STEARATE SE; POTASSIUM SORBATE; DIMETHICONE; GREEN TEA LEAF; CHAMOMILE; XANTHAN GUM; CETOSTEARYL ALCOHOL; LAVANDULA ANGUSTIFOLIA FLOWERING TOP; POLYSORBATE 60; MEDIUM-CHAIN TRIGLYCERIDES; CALENDULA OFFICINALIS FLOWER; GINKGO; ASIAN GINSENG; CETEARYL OLIVATE; SODIUM CHLORIDE; SORBITAN OLIVATE; SODIUM BENZOATE

Alba Botanica Sport Sunscreen Fragrance Free SPF 45

Active Ingredient

Avobenzone - 3.0%

Homosalate - 10.0%

Octocrylene - 10.0%

Octyl Salicylate - 5.0%

DOSAGE AND ADMINISTRATION

Apply liberally 15 minutes before sun exposure. Reapply after 80 minutes of swimming or sweating, immediately after towel drying and at least every 2 hours.

PURPOSE

Sunscreen

WARNINGS

For external use only. Do not use on damaged or broken skin. When using this product keep out of eyes. Rinse with water to remove. Stop use and ask a doctor if skin rash occurs.

Keep out of reach of children. If swallowed get medical help or contact Poison Center right away.

INACTIVE INGREDIENT

Water, Glycerin, Glyceryl Stearate SE, Cetyl Alcohol, Dimethicone, Cetearyl Alcohol, VP/Hexadecene Copolymer, Caprylic/Capric Triglyceride, Aloe Barbadensis Leaf Juice(1), Camellia Sinensis Leaf Extract (1), Chamomilla Recutita (Matricaria) Flower Extract (1), Calendula Officinalis Flower Extract (1), Lavandula Angustifolia (Lavender) Extract (1), Ginkgo Biloba Leaf Extract, Panax Ginseng Root Extract, Cetearyl Alcohol, Cetearyl Olivate, Polysorbate 60, Sodium Chloride, Sodium Stearoyl Glutamate, Sorbitan Olivate, Tocopheryl Acetate, Xanthan Gum, Alcohol (1), Benzyl Alcohol, Potassium Sorbate, Sodium Benzoate.

(1) Certified Organicf Ingredient

INDICATIONS AND USAGE

Helps prevents sunburns. If used as directed with other sun protection measures, decreases risk of skin cancer and early skin aging caused by sun exposure. Skin Protection Measures: Spending time in the sun increases your risk of skin cancer and early skin aging. To decrease risk, regularly use sunscreen with Broad Spectrum SPF 15 or higher and other protective measures including: limit time in sun, especially from10am to 2pm, and wear long sleeved shirts, pants, hats and sunglases.